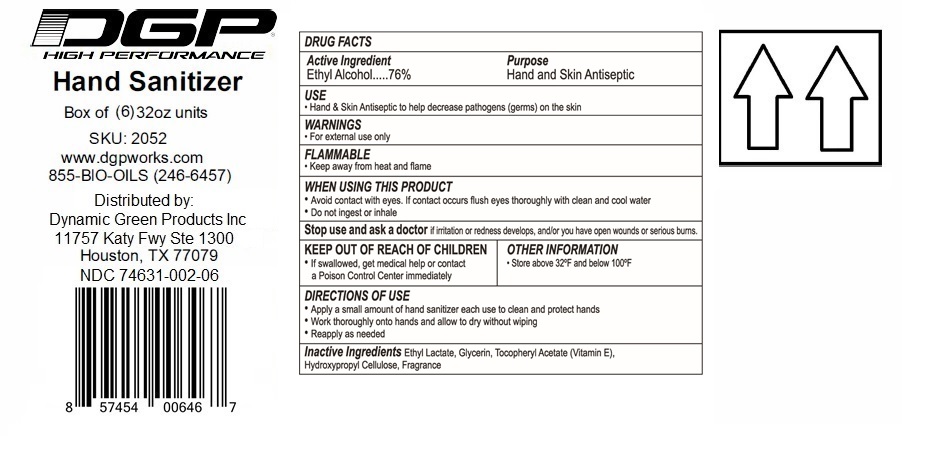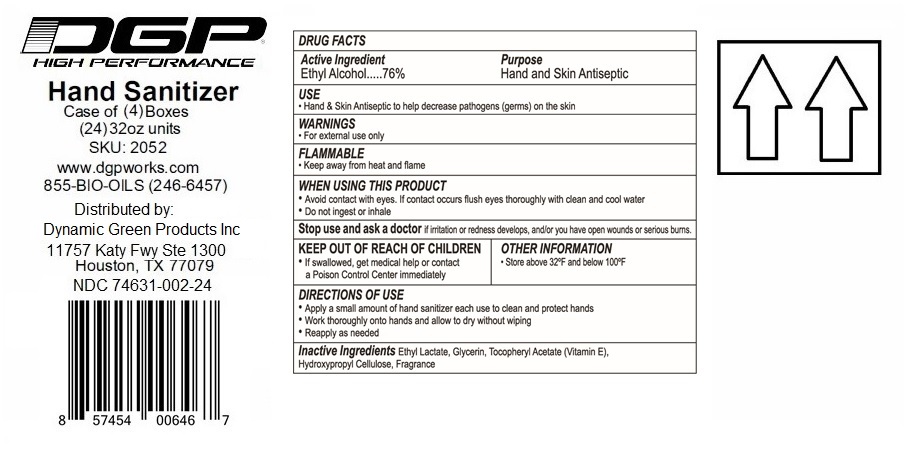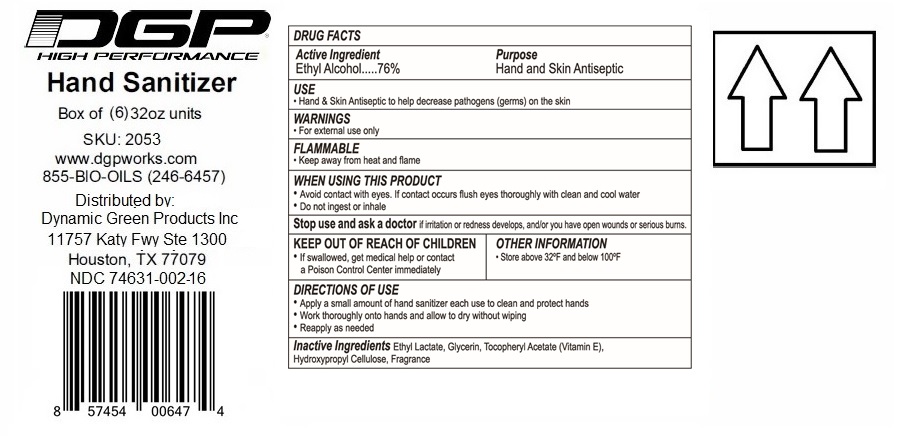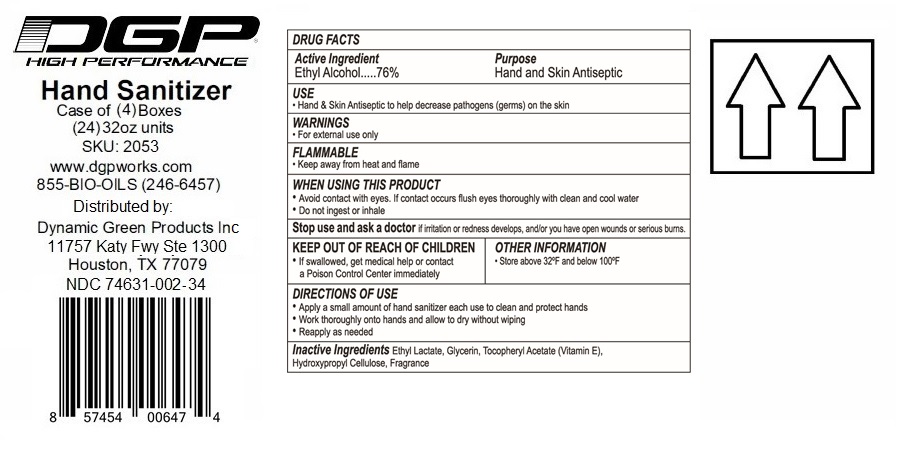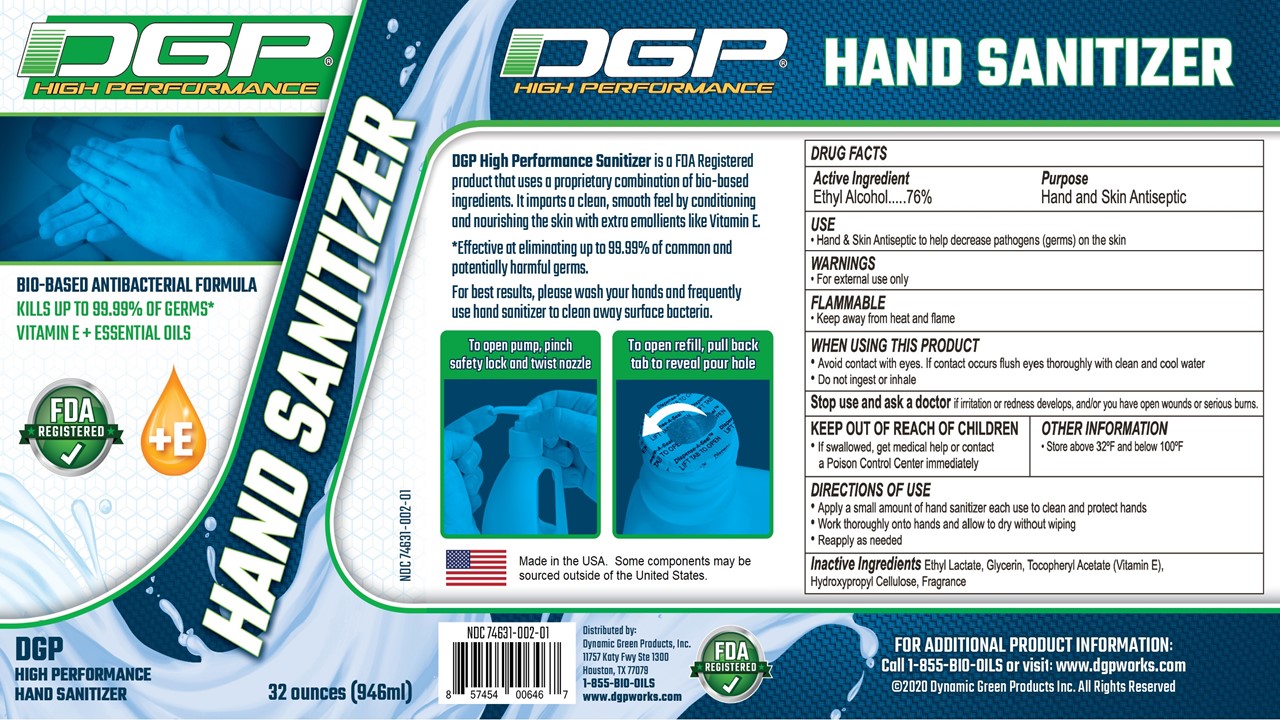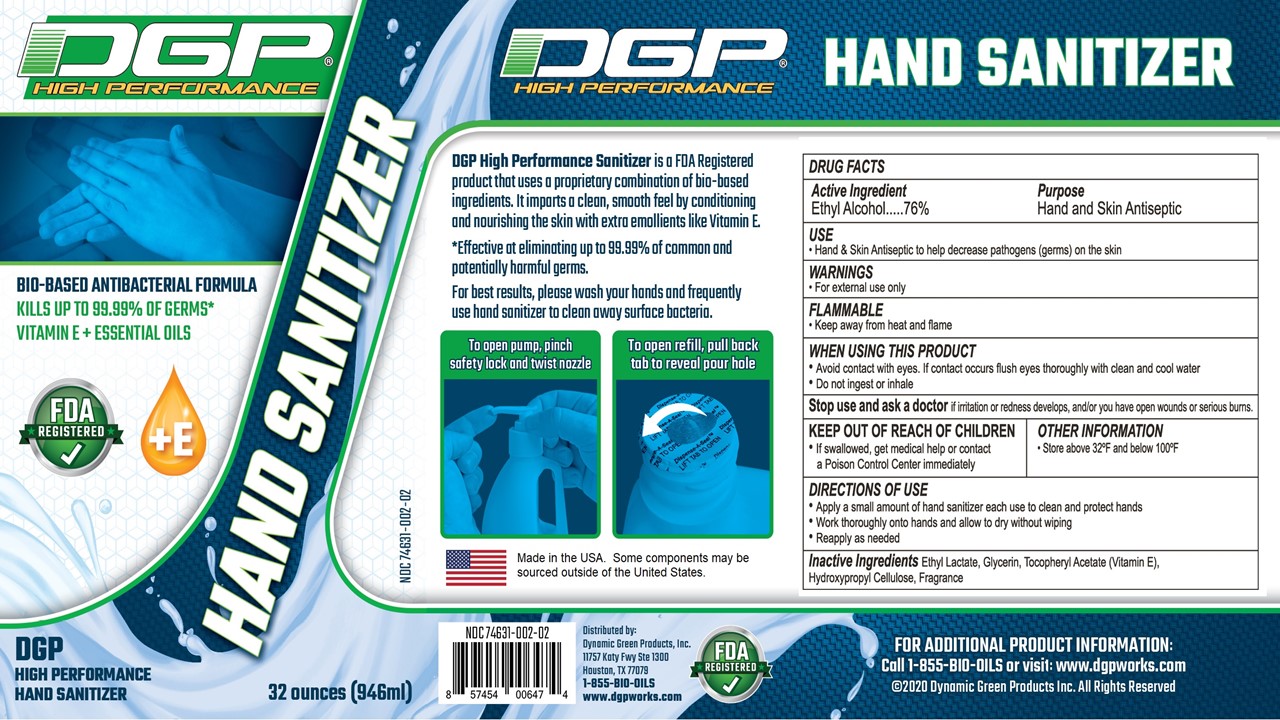 DRUG LABEL: DGP High Performance Hand Sanitizer
NDC: 74631-002 | Form: GEL
Manufacturer: Dynamic Green Products, Inc.
Category: otc | Type: HUMAN OTC DRUG LABEL
Date: 20211206

ACTIVE INGREDIENTS: ALCOHOL 76 mL/100 mL
INACTIVE INGREDIENTS: GLYCERIN; ALPHA-TOCOPHEROL ACETATE; HYDROXYPROPYL CELLULOSE (110000 WAMW); ETHYL LACTATE

Drug Facts

Active ingredient

Ethyl Alcohol 76%

Purpose

Hand & Skin Antiseptic

INDICATIONS AND USAGE

Hand & Skin Antiseptic to help decrease pathogens (germs) on the skin

WARNINGS

For external use only

Flammable: Keep away from heat and flame

WHEN USING

* Avoid contact with eyes. If contact occurs flush eyes thoroughly with clean and cool water

* Do not ingest or inhale

Stop use and ask a doctor

* If irritation or redness develops, and/or you have open wounds or serious burns.

Stop use

* If irritation or redness develops

* Have open wounds or serious burns

Keep out of reach of children

* If swallowed, get medical help or contact a Poison Control Center immediately

Directions

* Apply a small amount of hand sanitizer each use to clean and protect hands

* Work thoroughly onto hands and allow to dry without wiping

* Reapply as needed

Inactive ingredients

Ethyl Lactate, Glycerin, Tocopheryl Acetate (Vitamin E), Hydroxypropyl Cellulose, Fragrance

Principal Display Panel

DGP (R) High Performance Hand Sanitizer

Bio-based Antibacterial Formula

Vitamin E + Essential Oils

To open pumps, pinch safety lock and twist nozzle

To open refill, pull back tab to reveal pour hole

All ingredients are made in the USA

The packaging is sourced in the USA

The hand pump is non-domestic sourced

Distributed by:

Dynamic Green Products, Inc.

11757 Katy Fwy Ste 1300

Houston, TX 77079

For additional Product information: Call 855-BIO-OILS or visit www.dgpworks.com

(C) Dynamic Green Products Inc. All Rights Reserved

XX oz (zzzmL) NDC 74631-001-xx